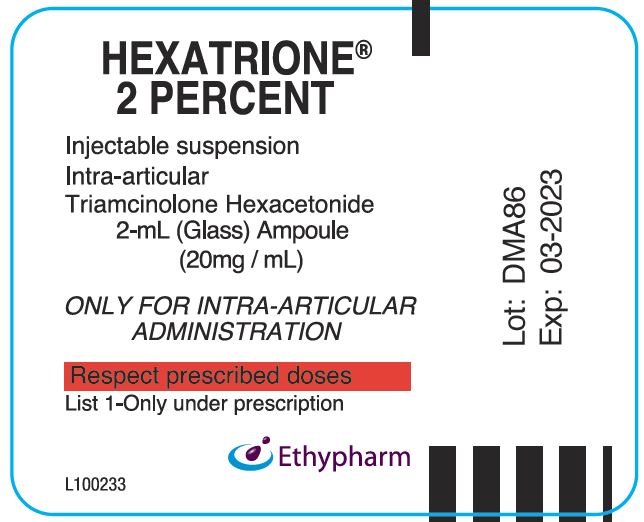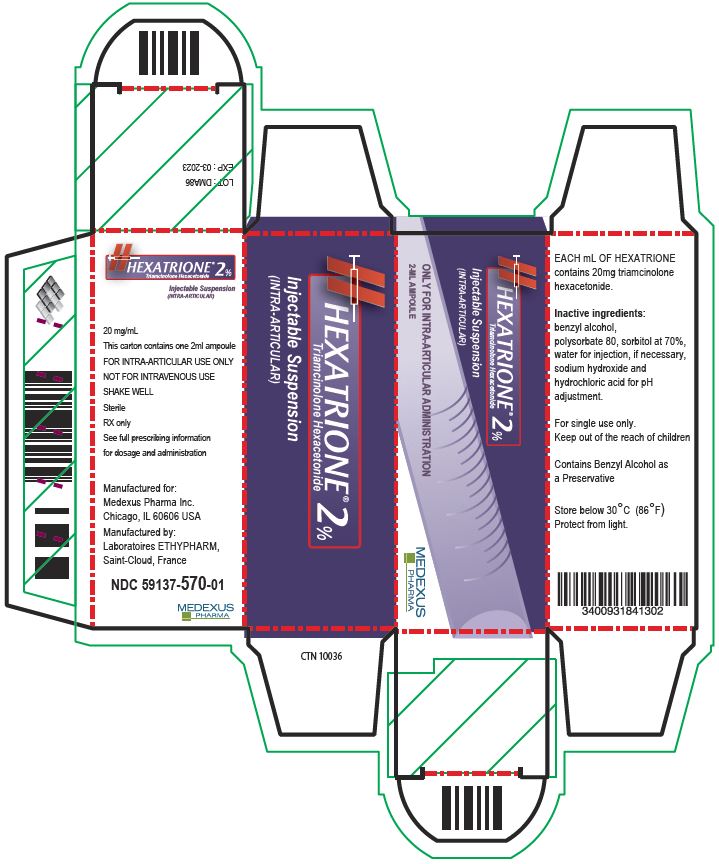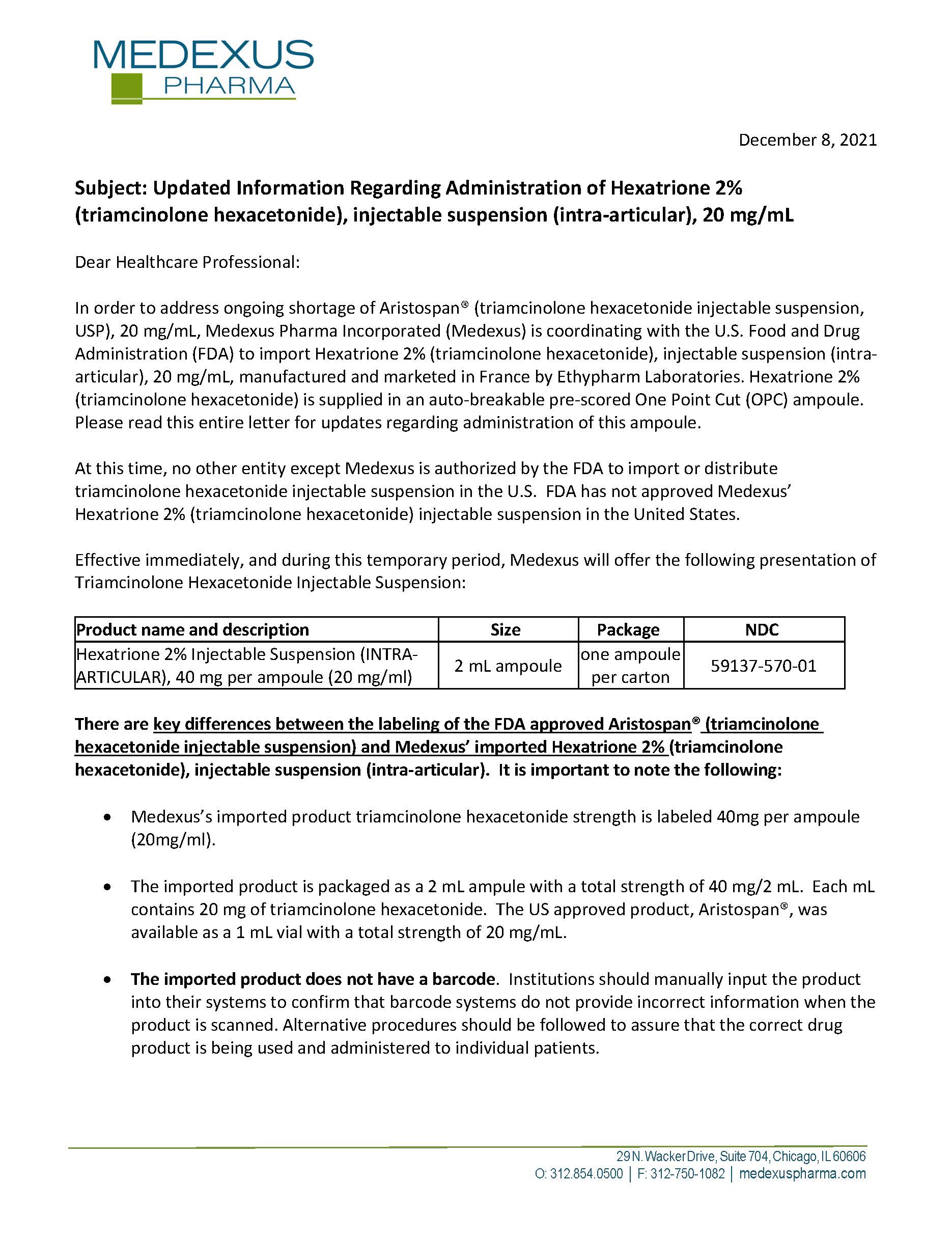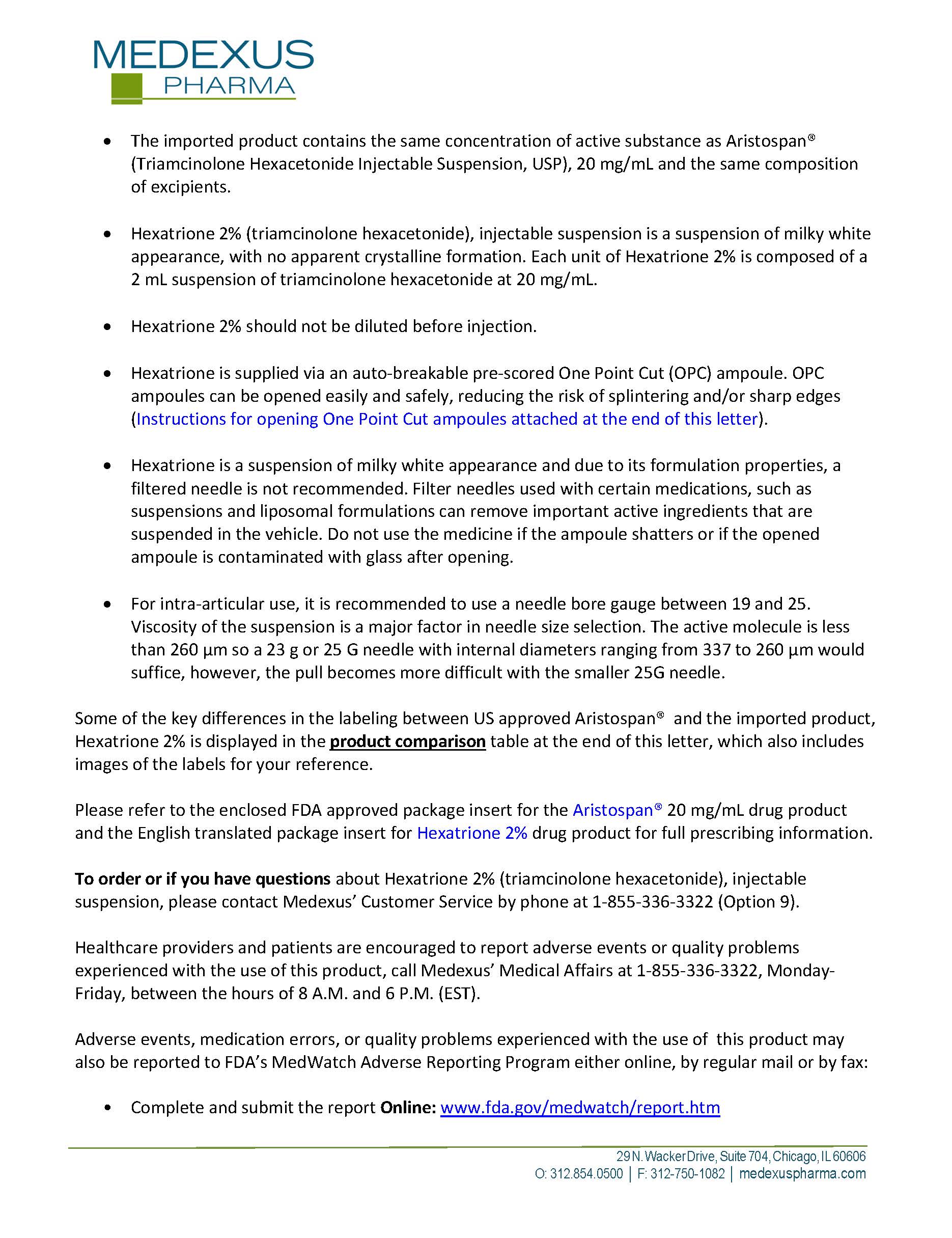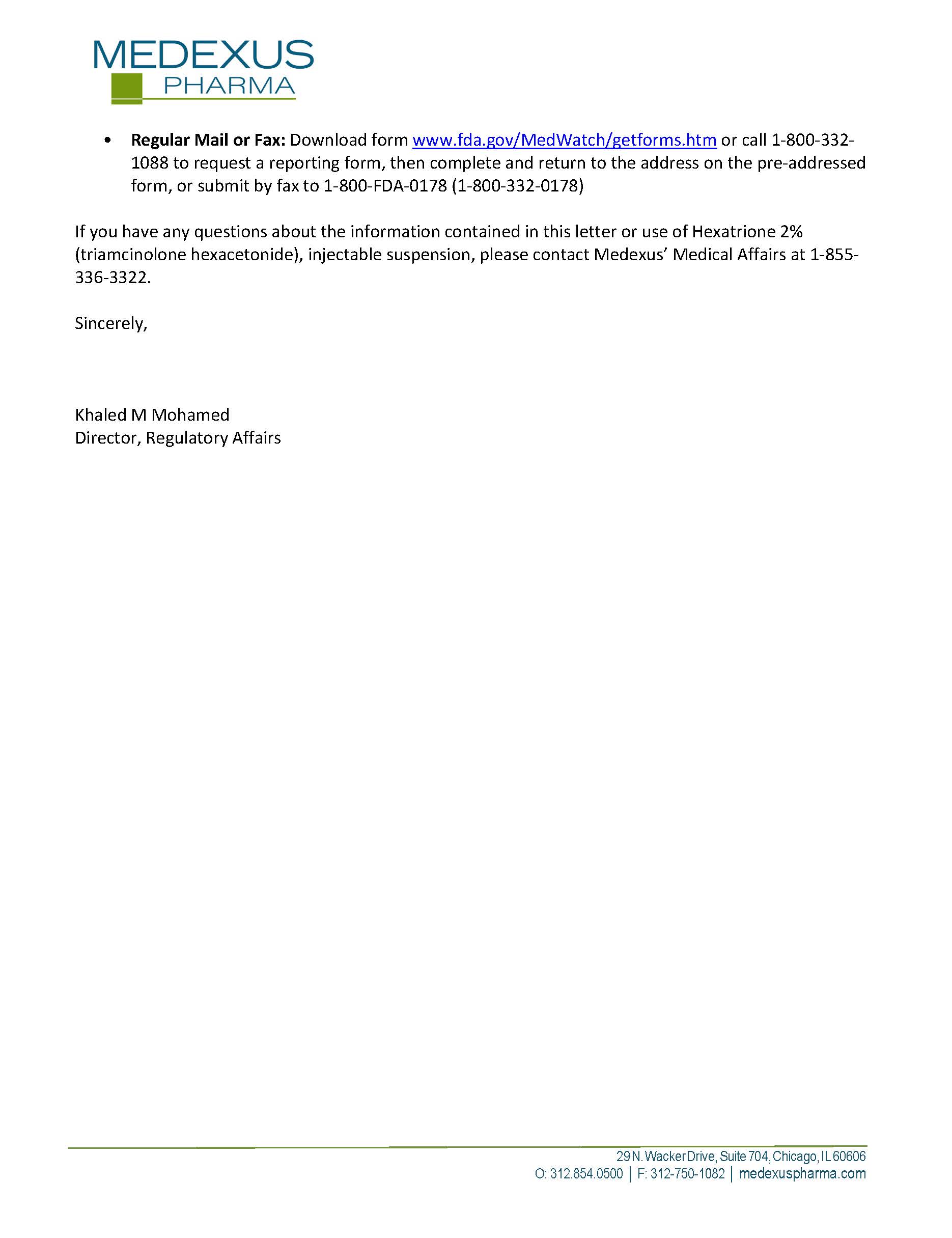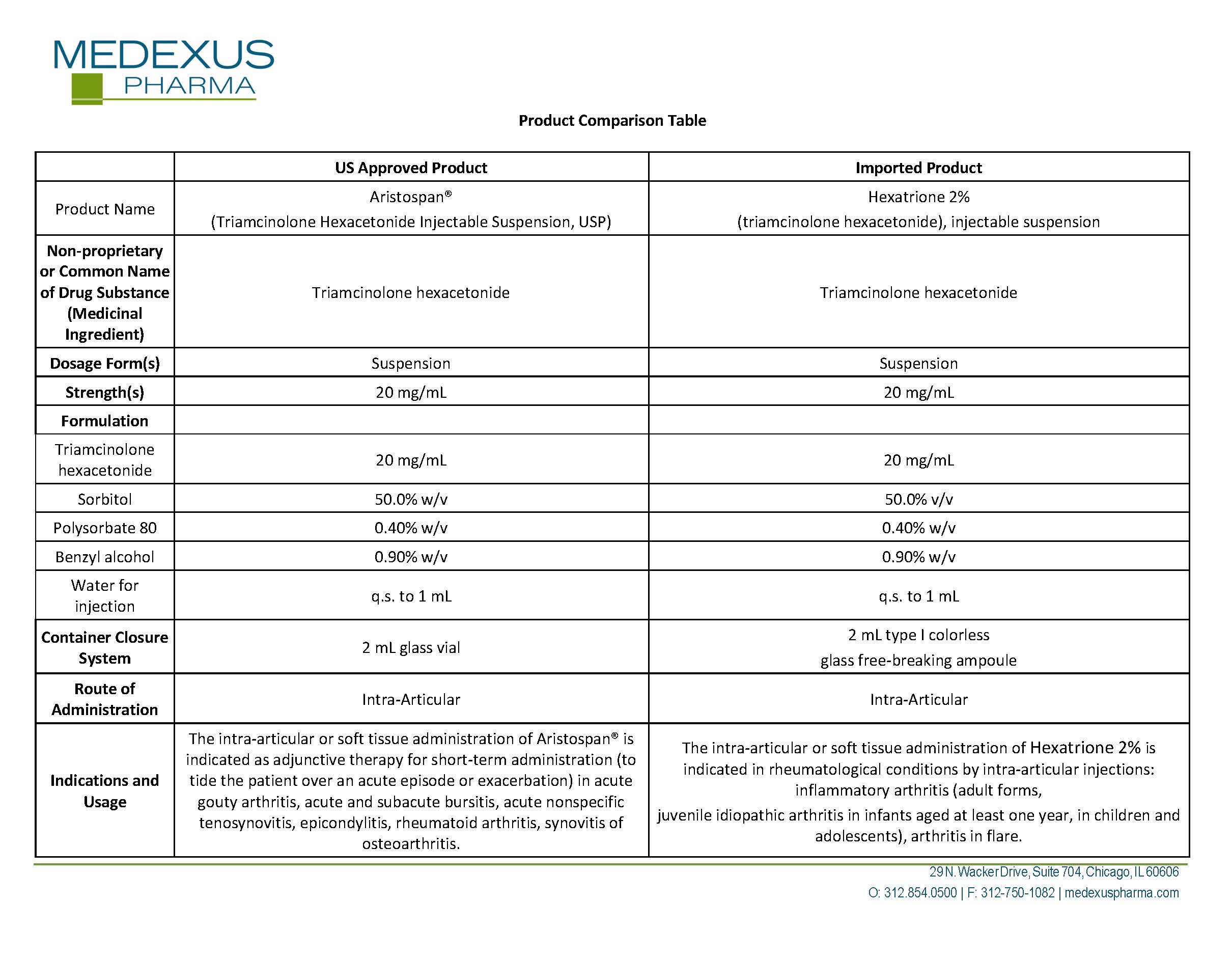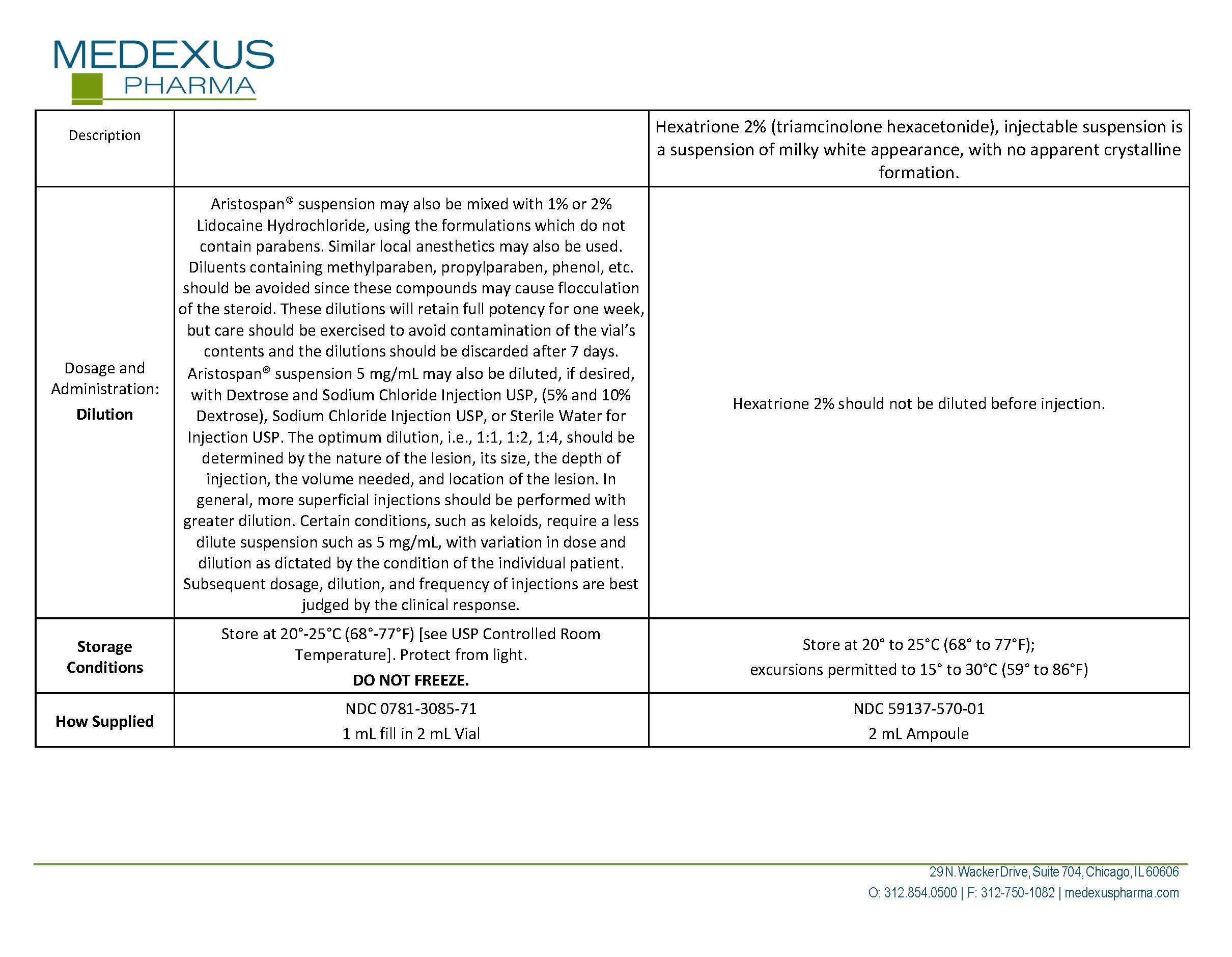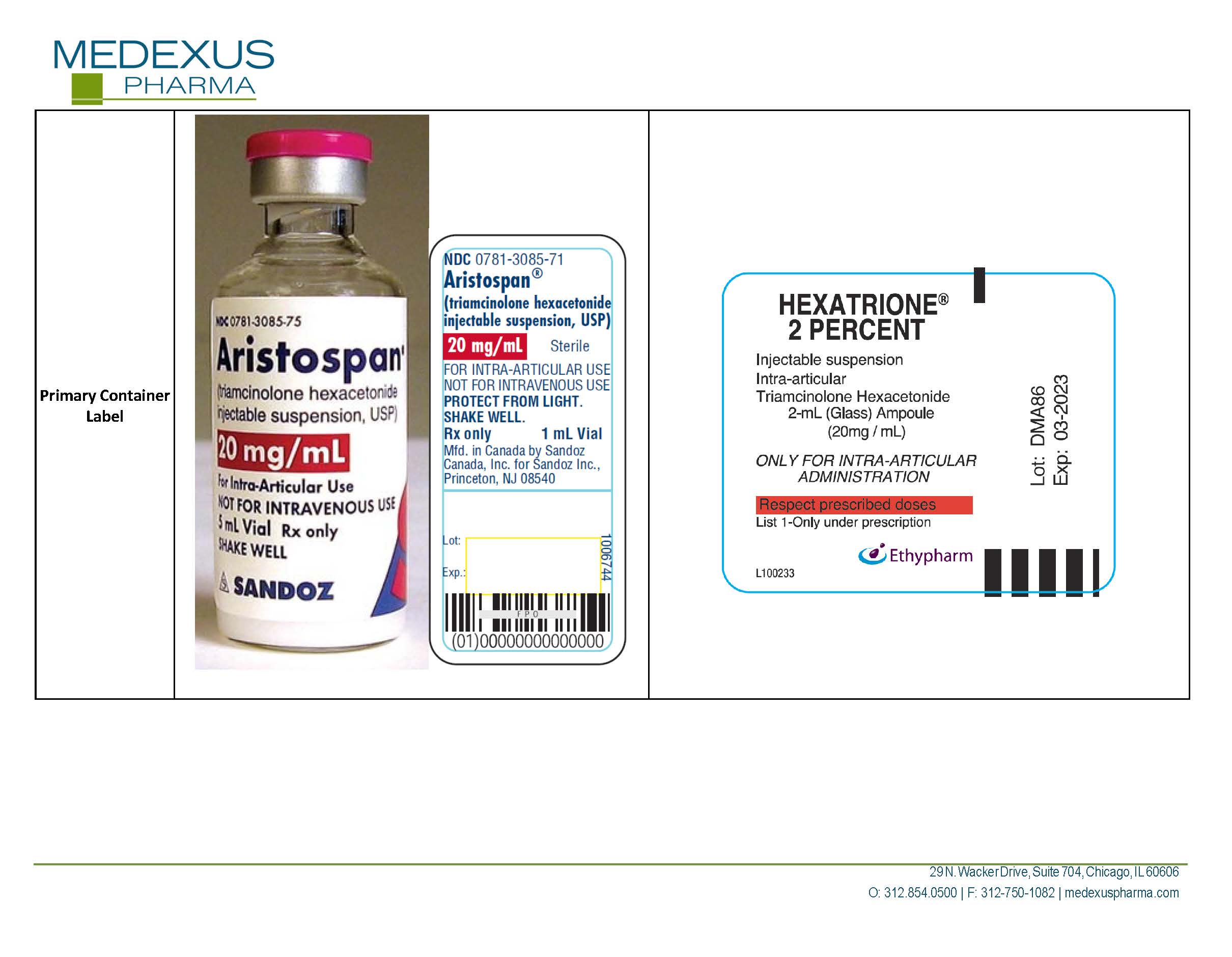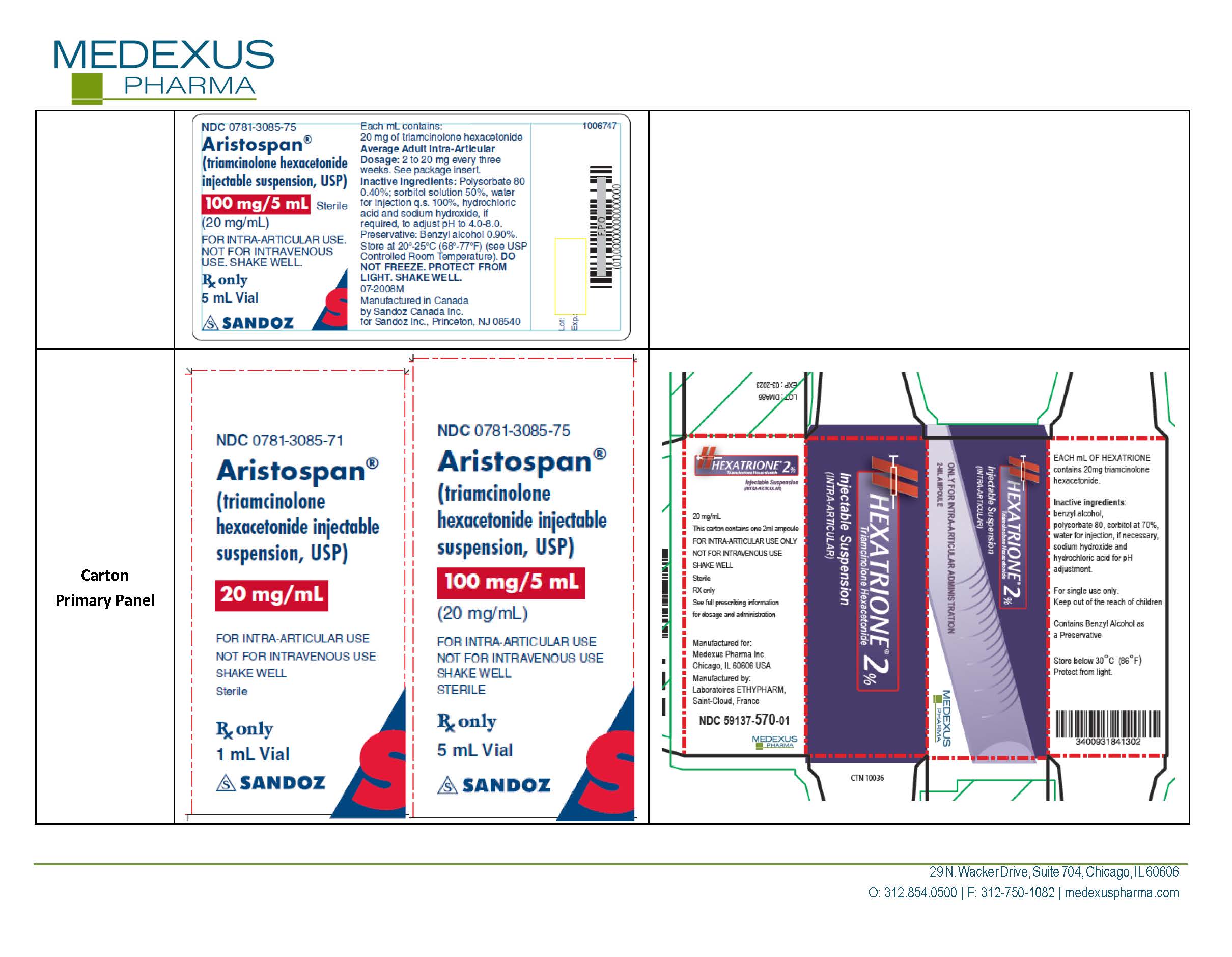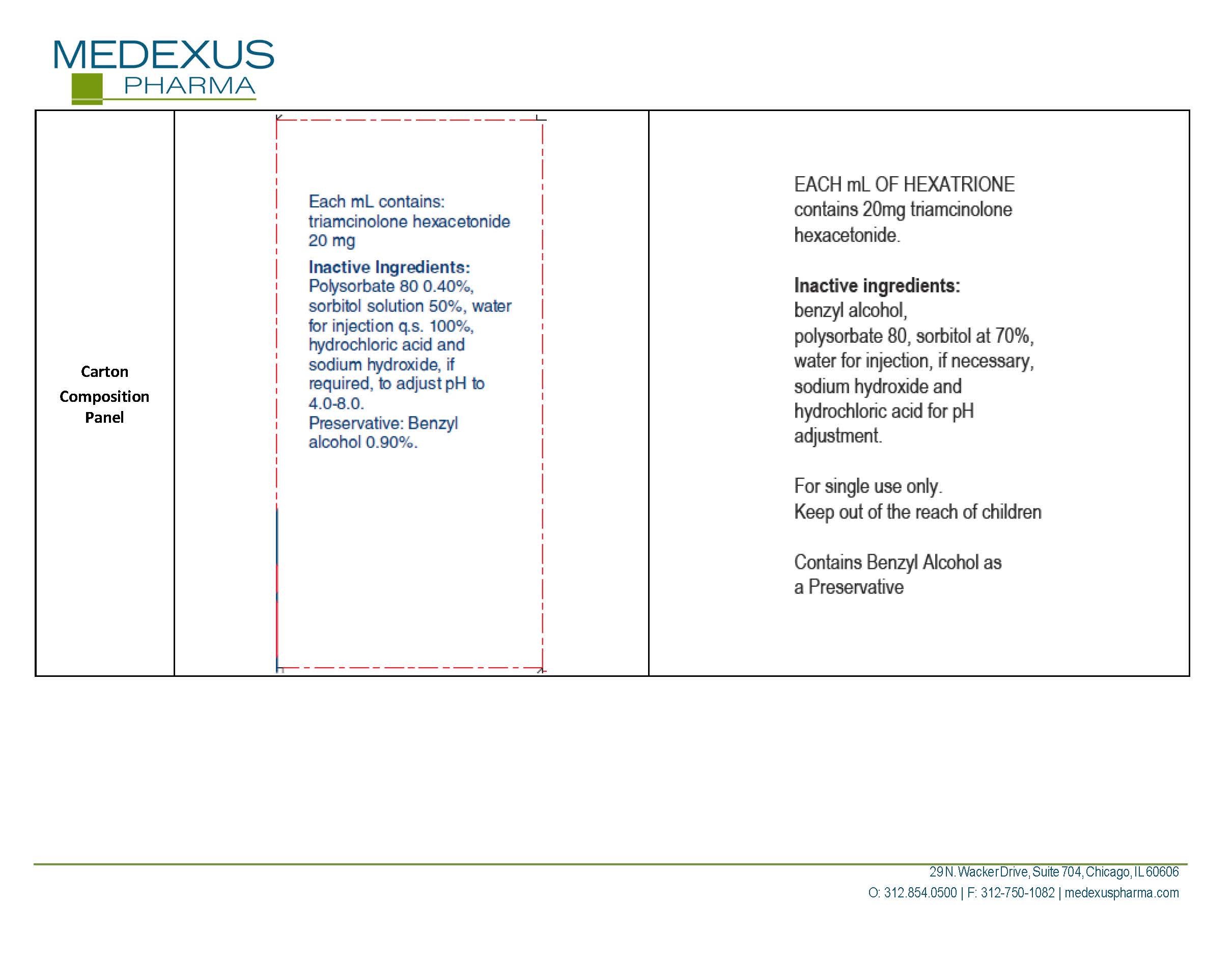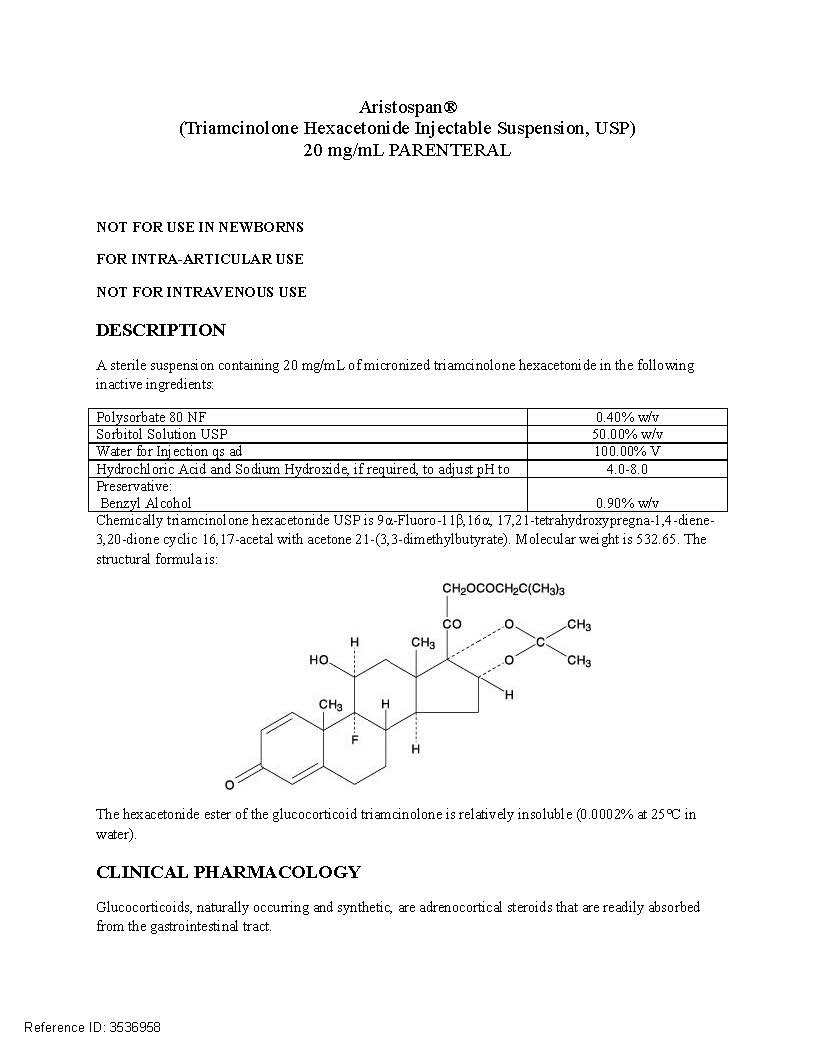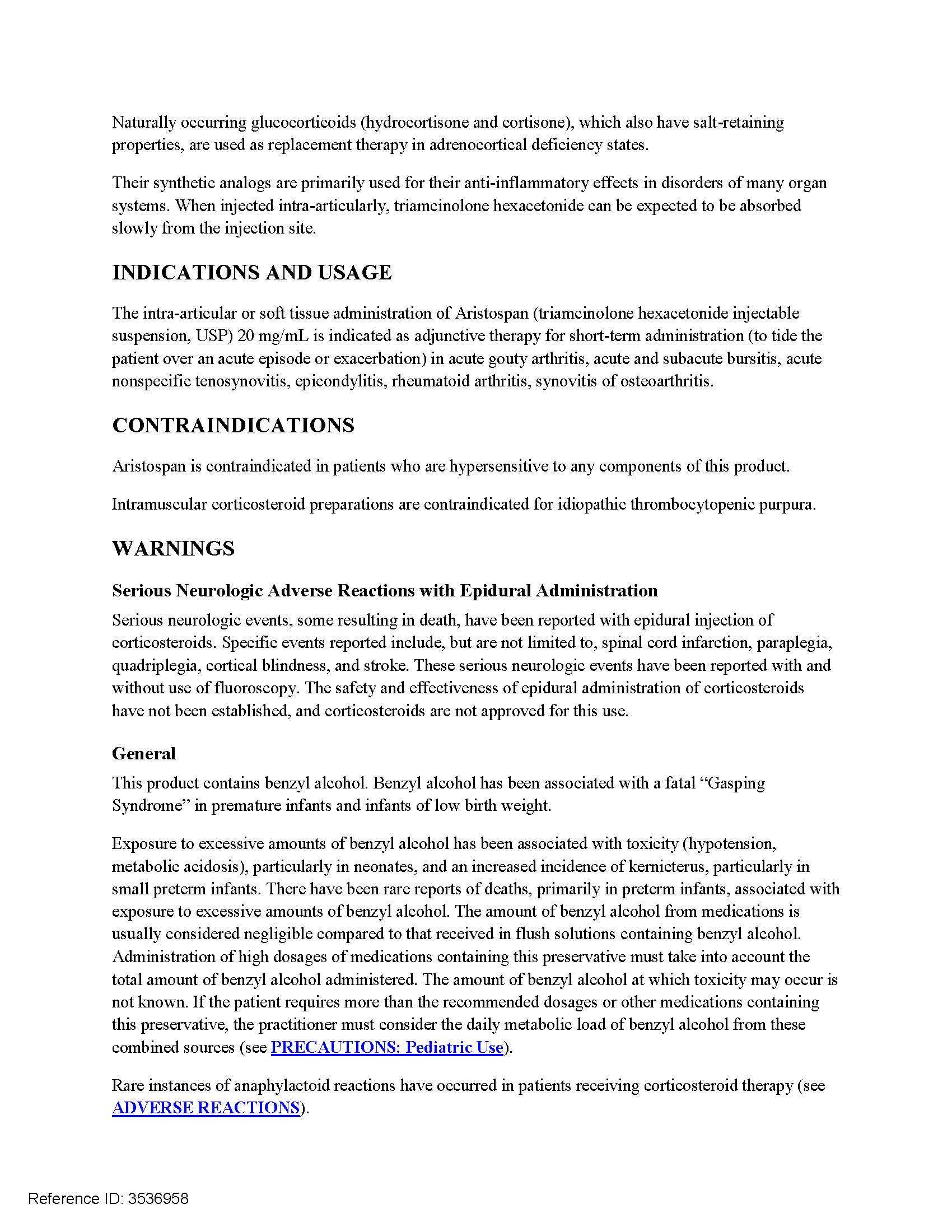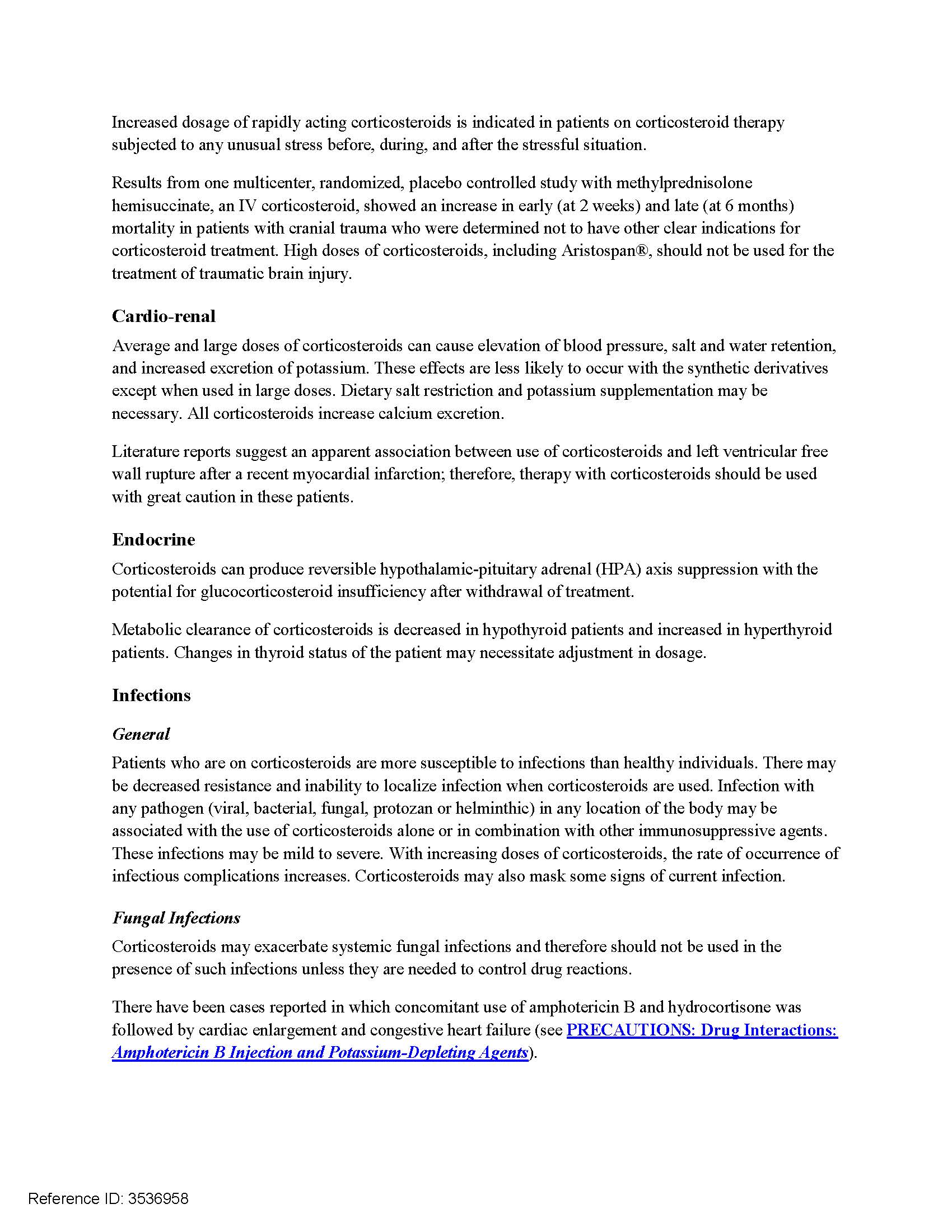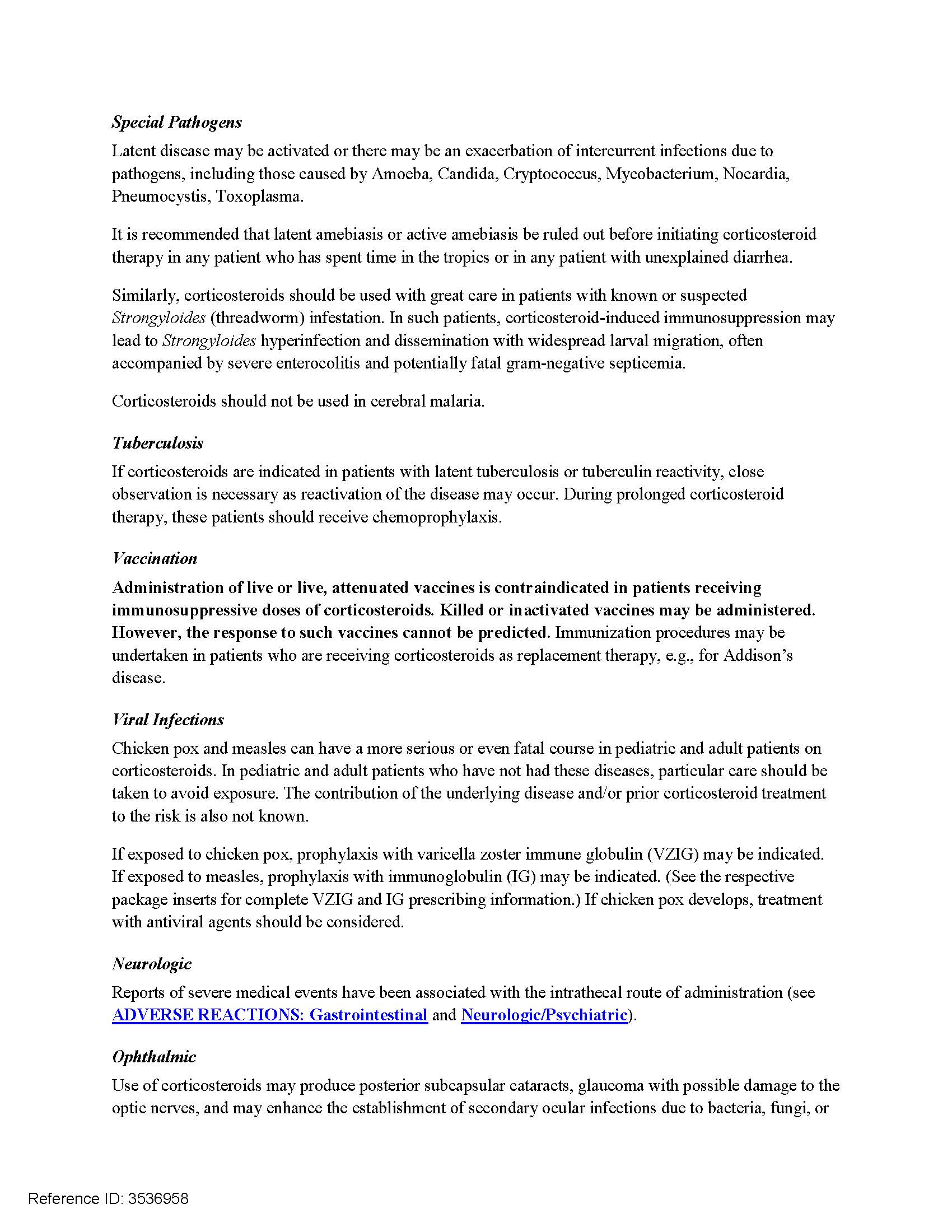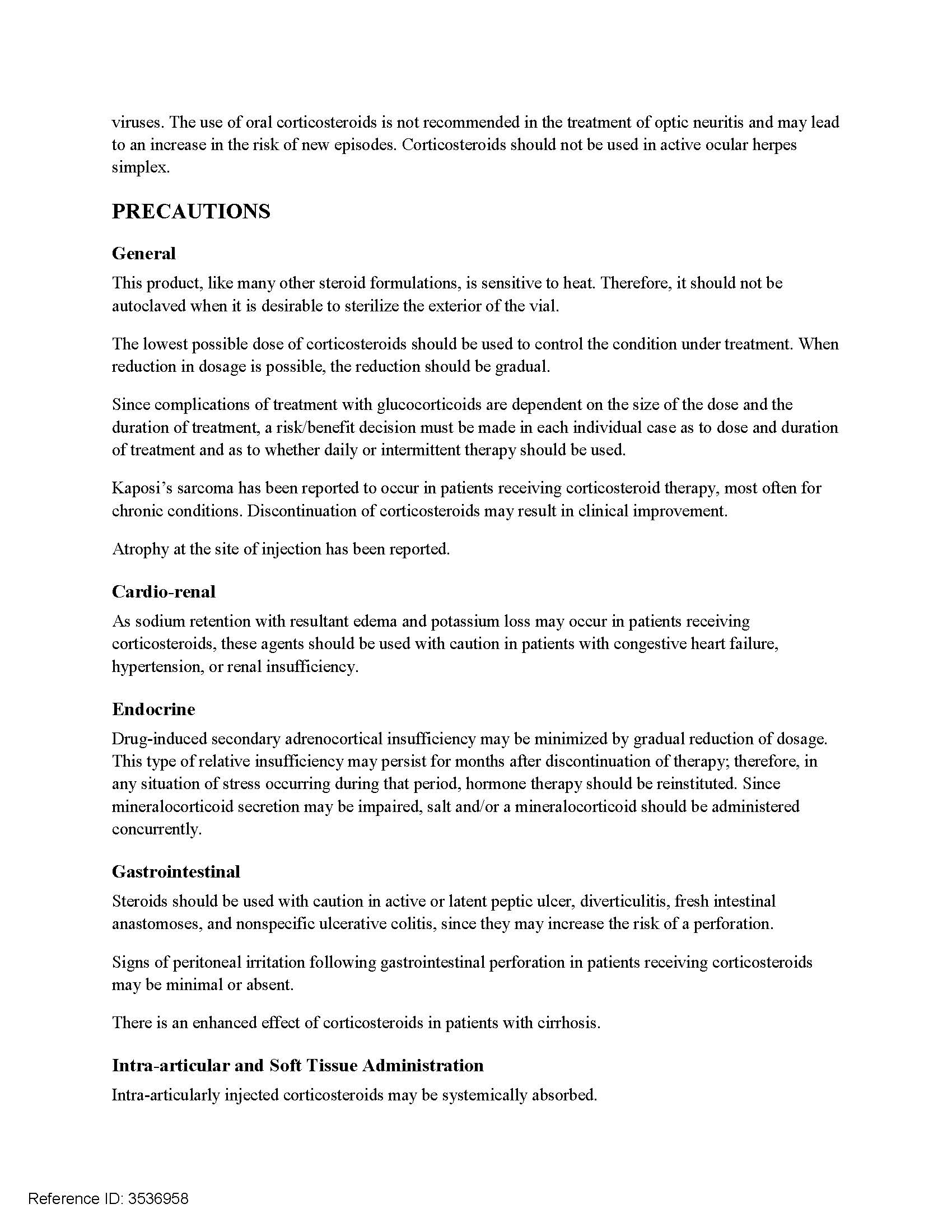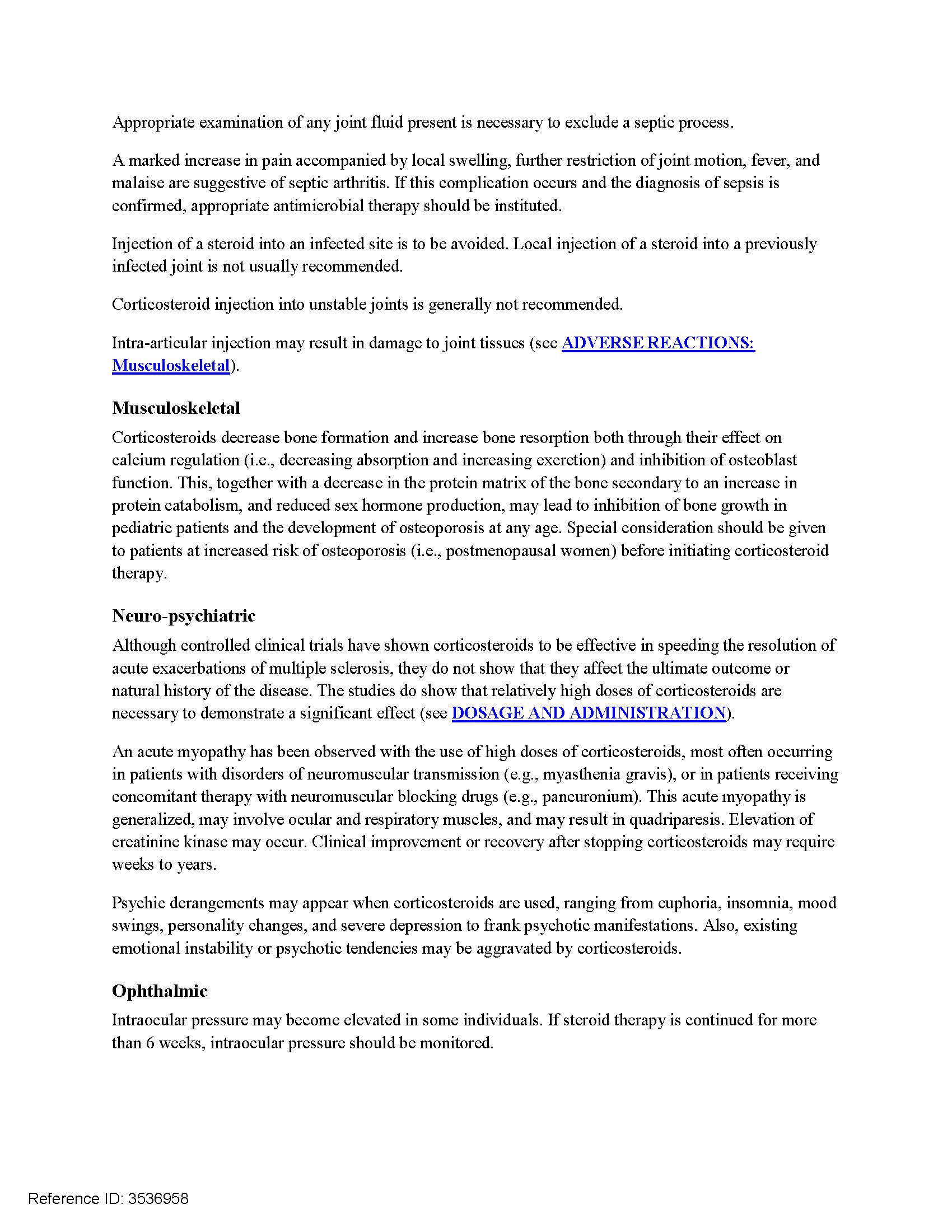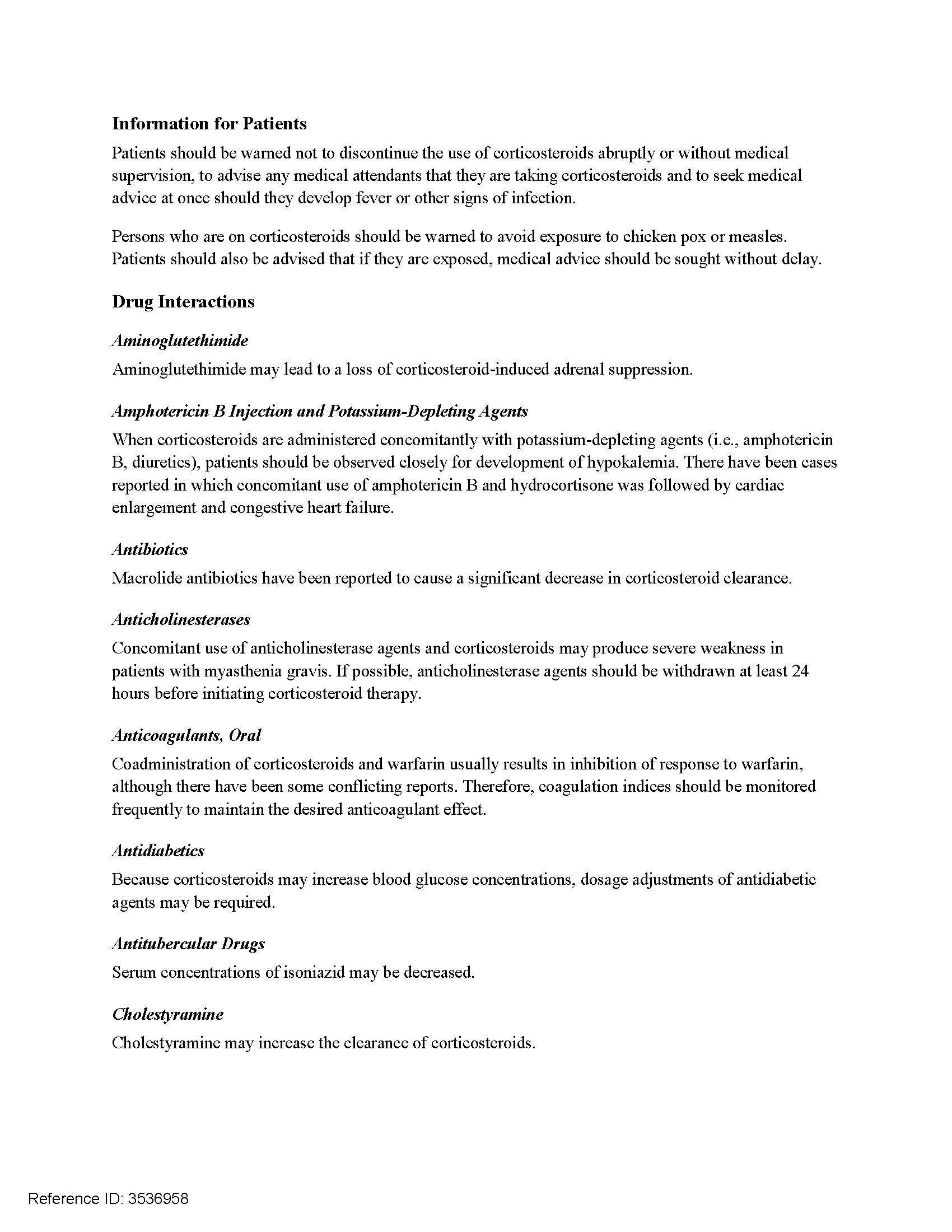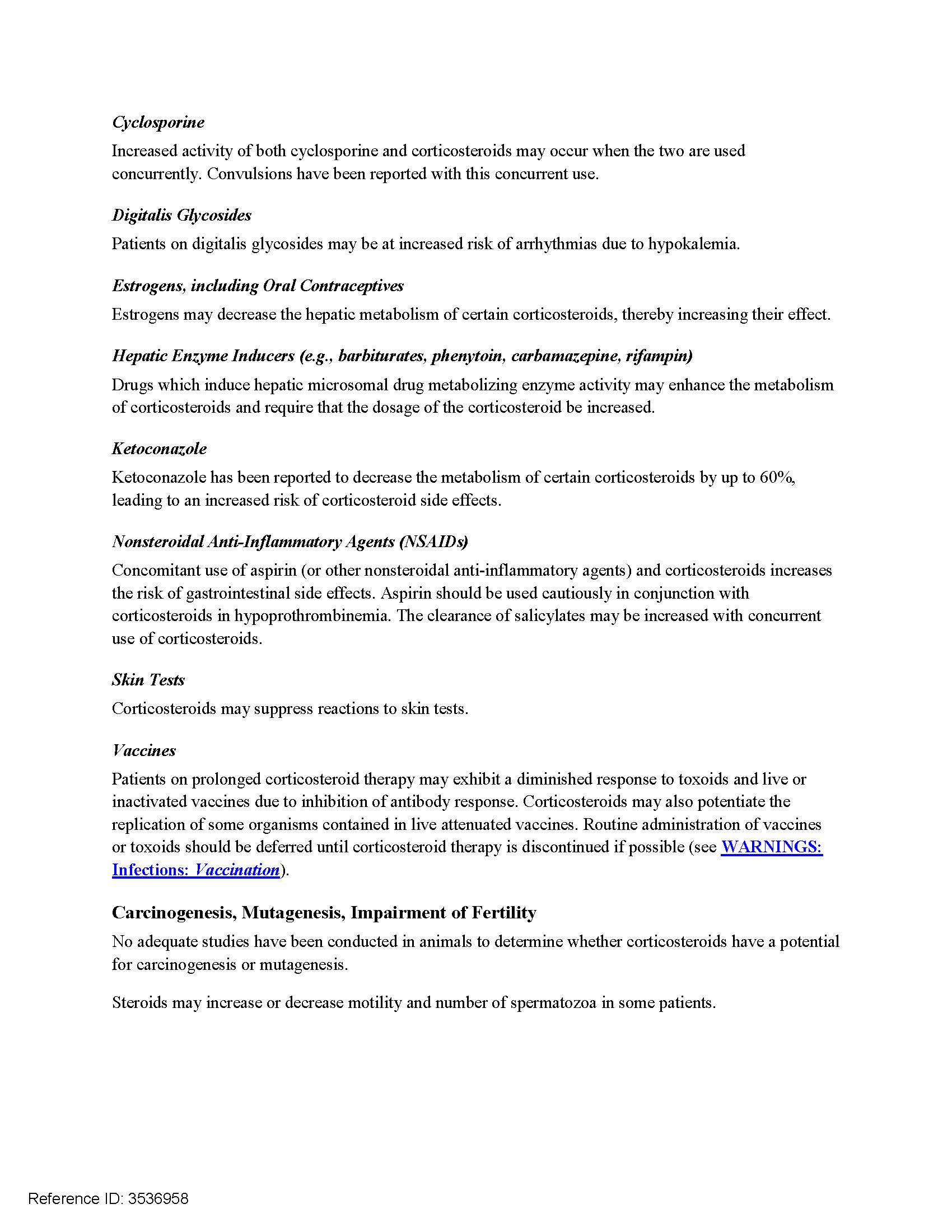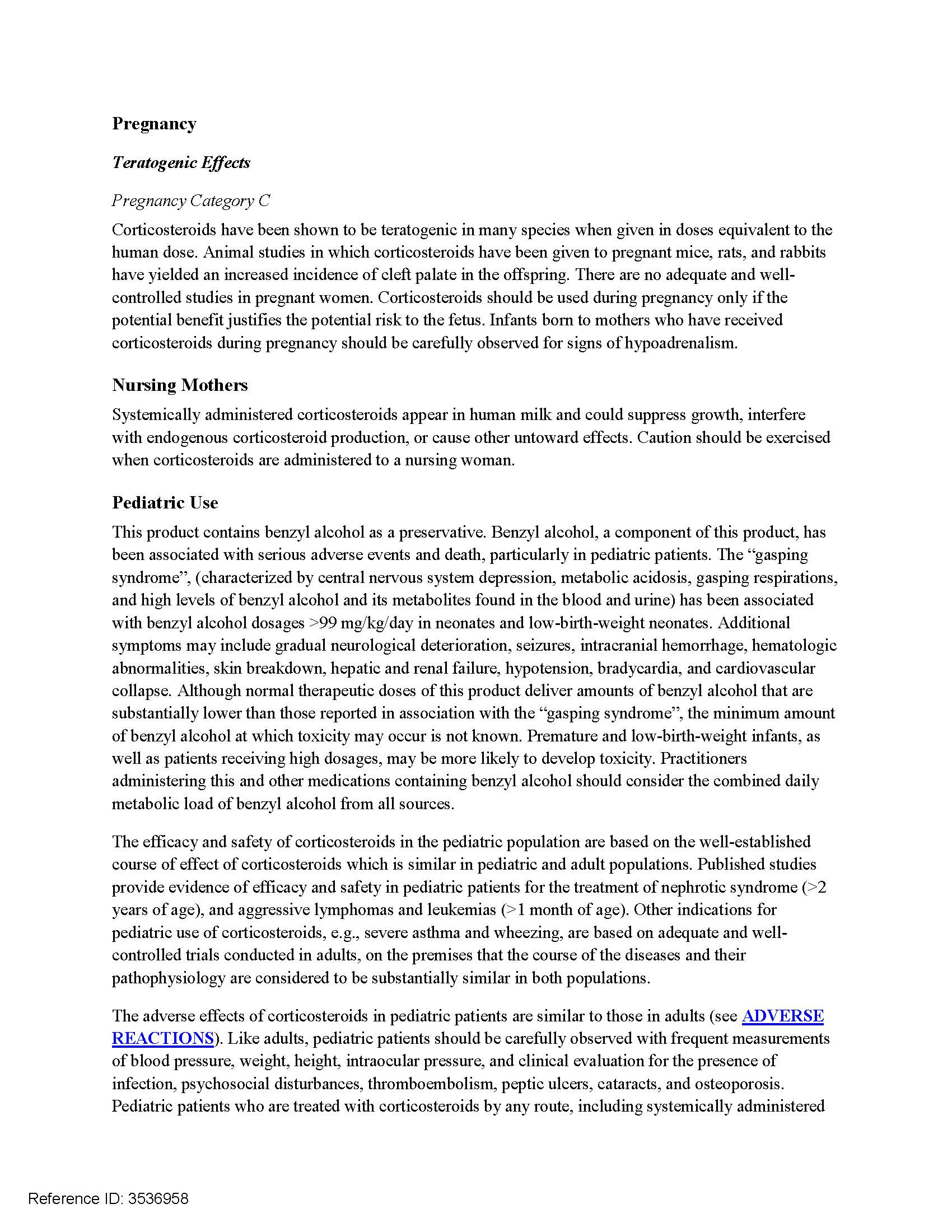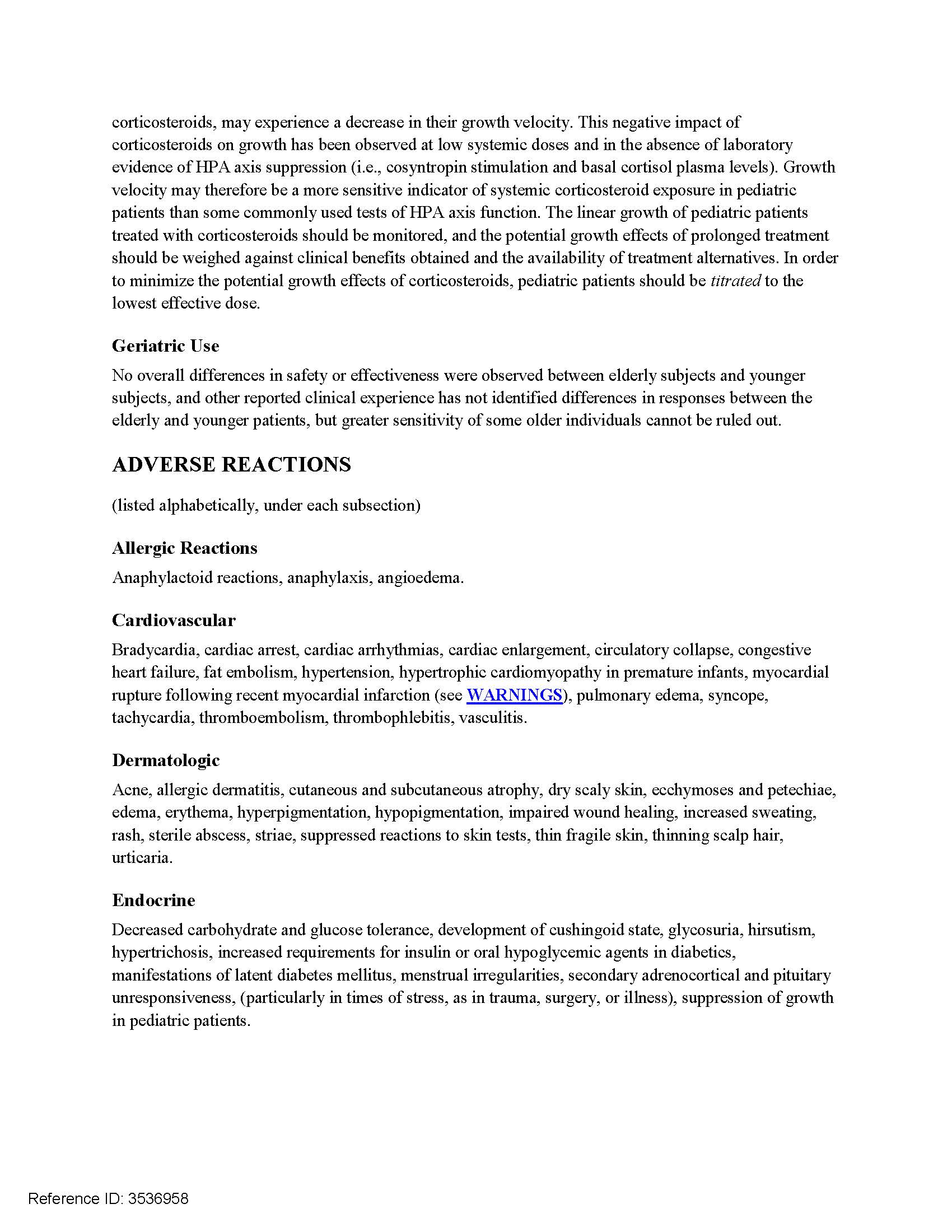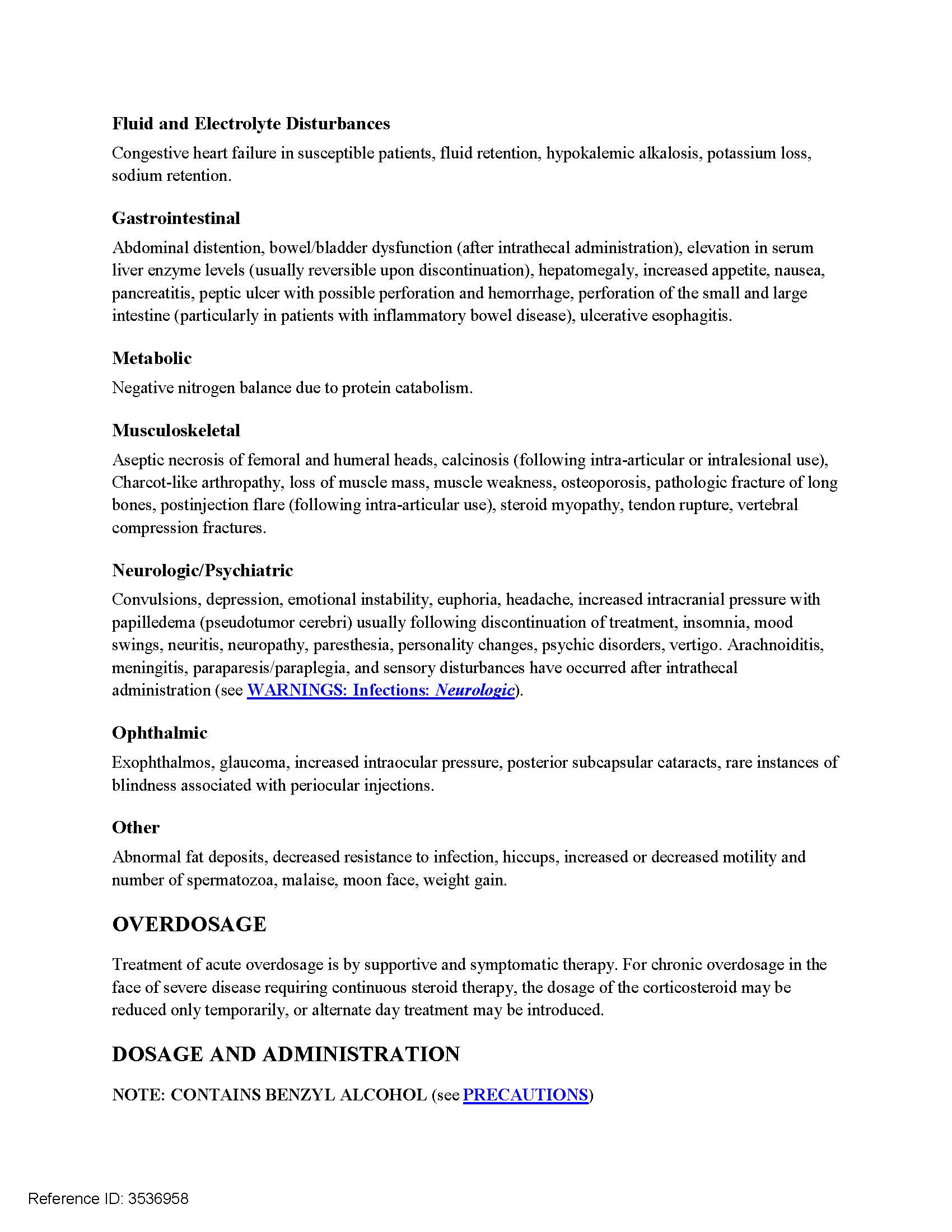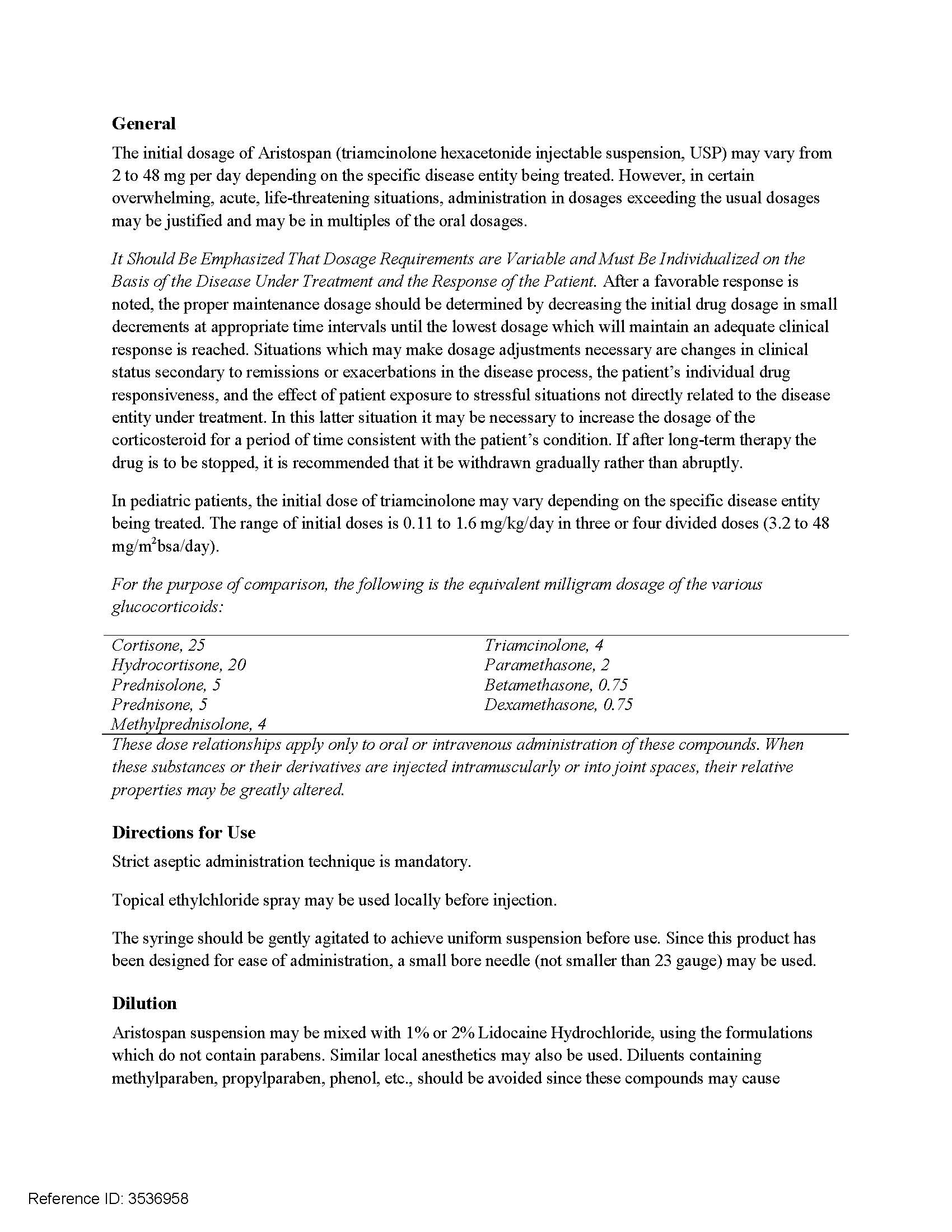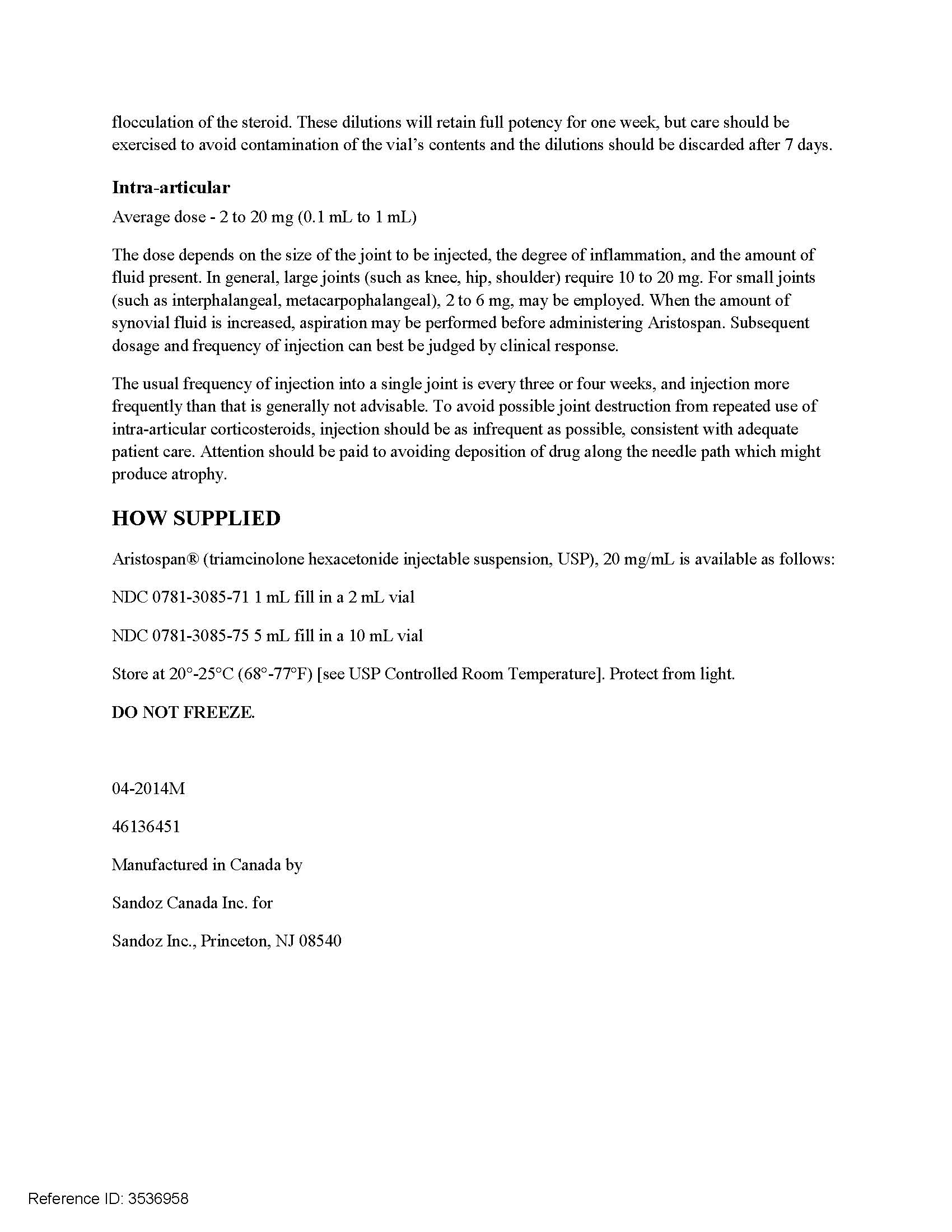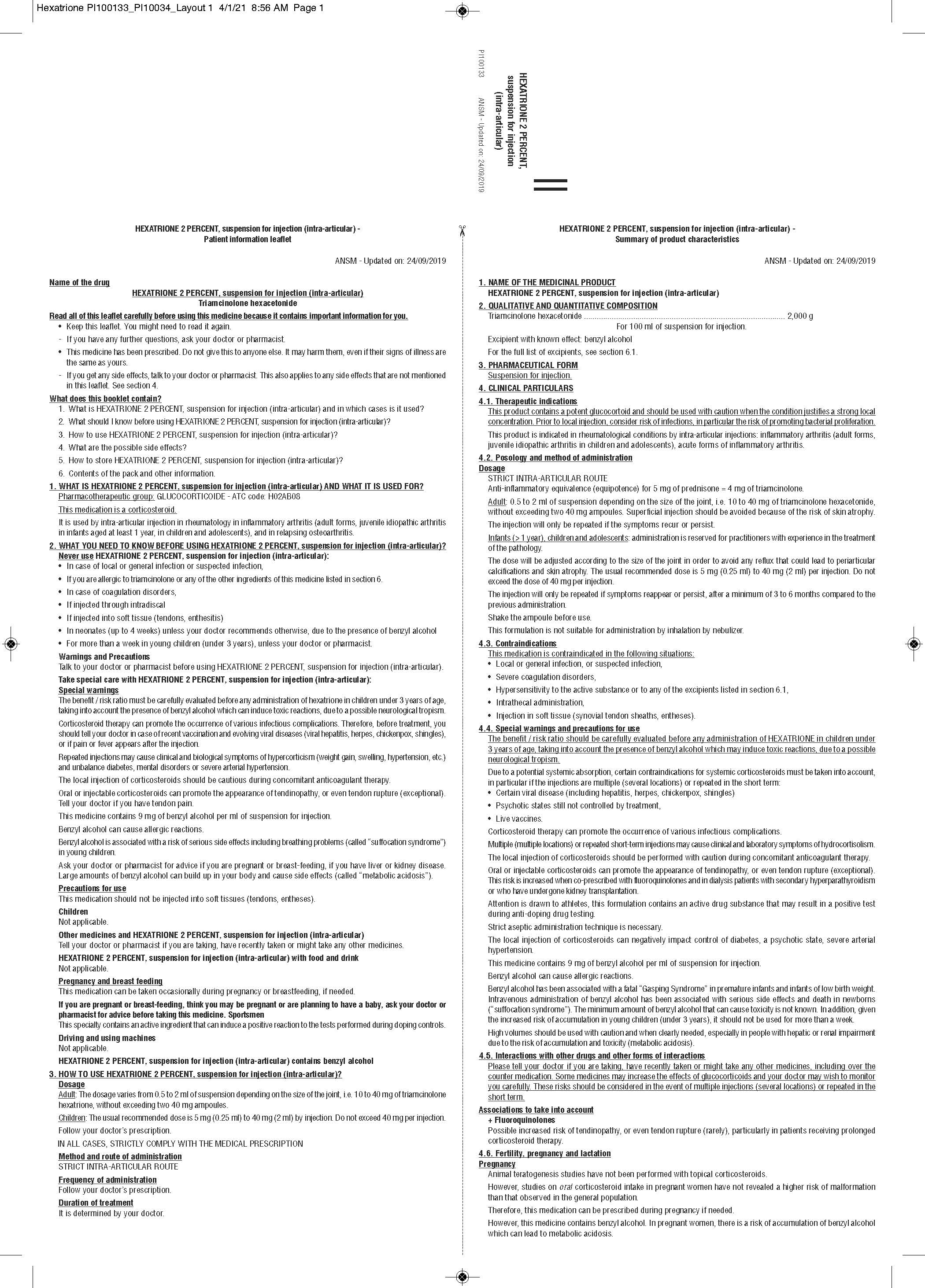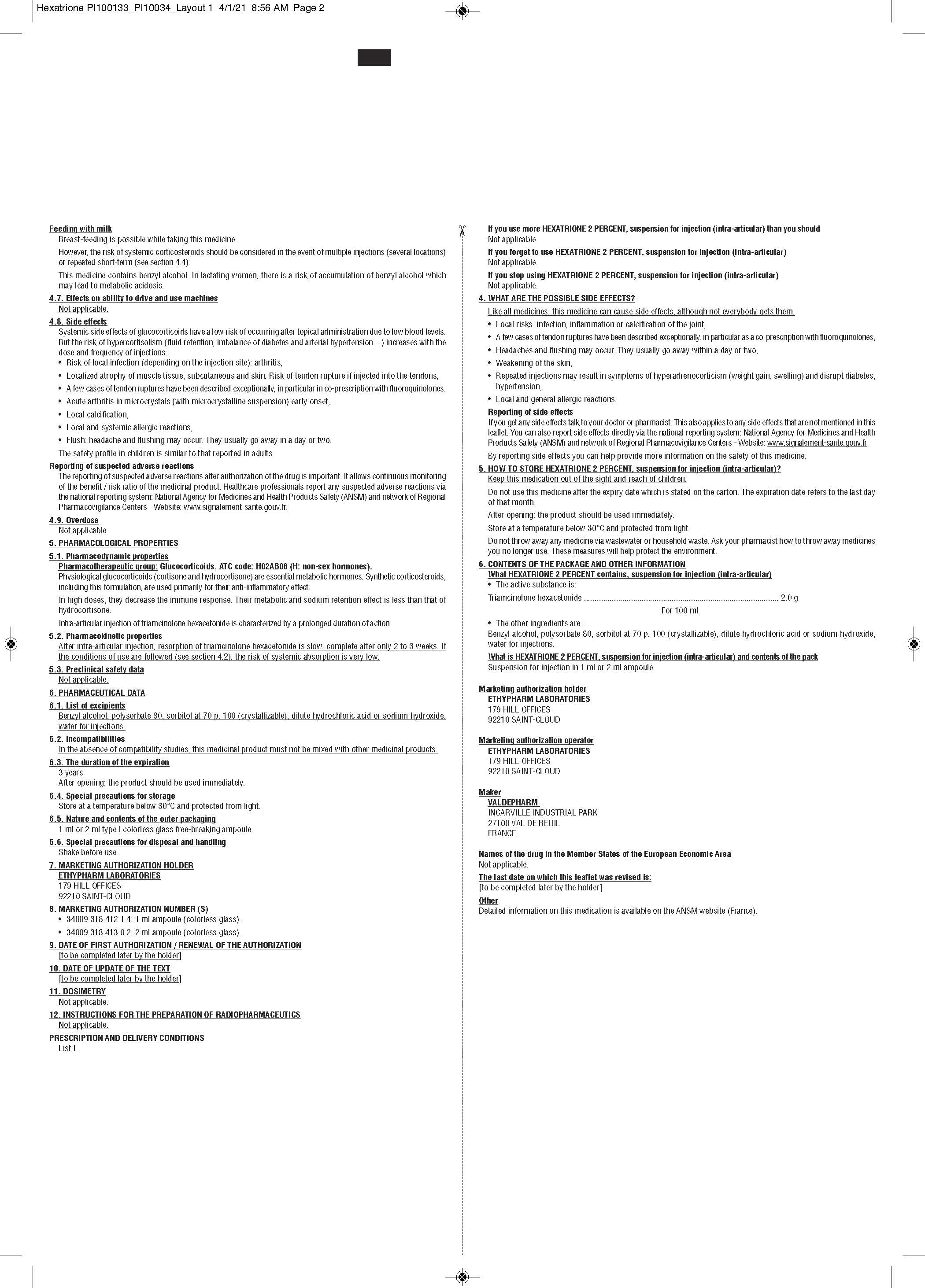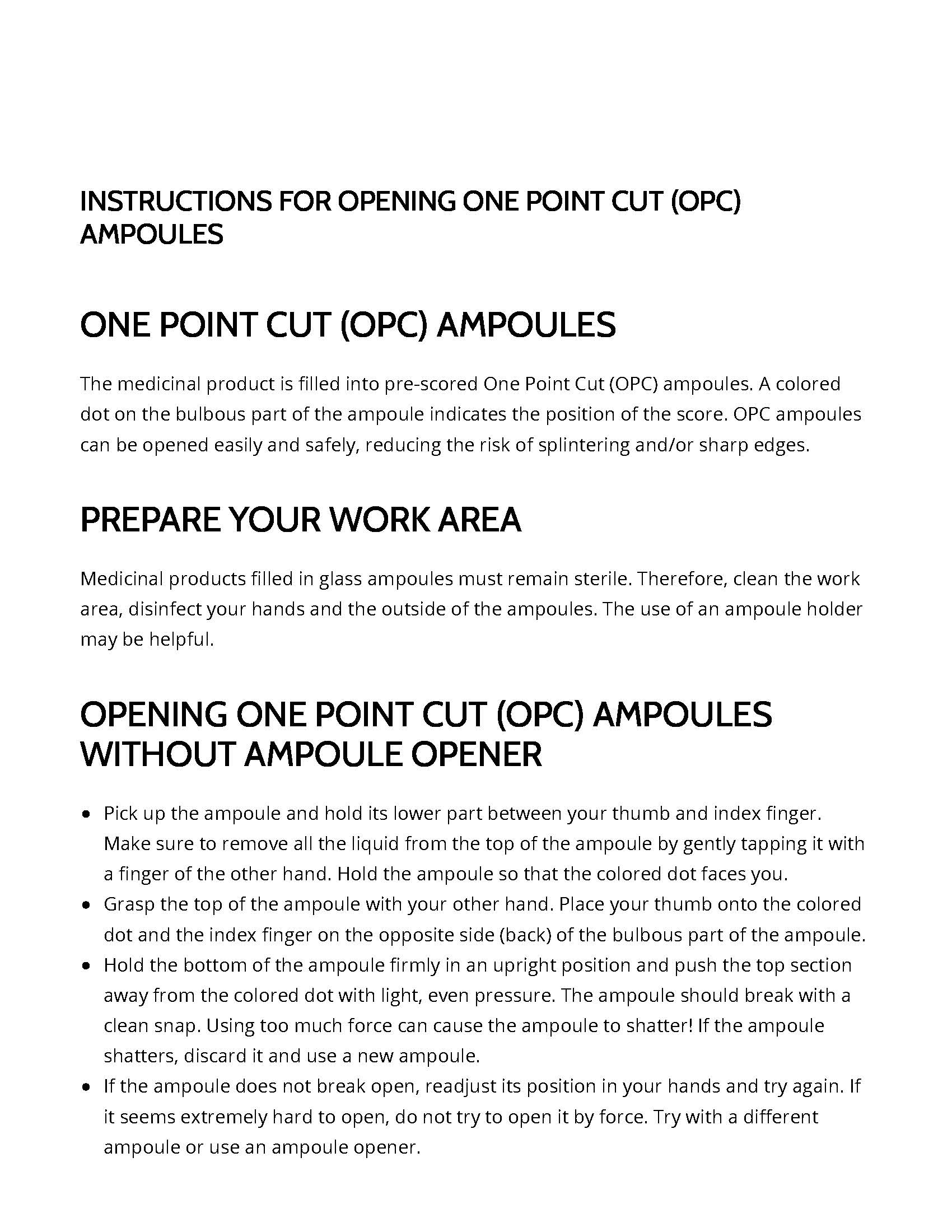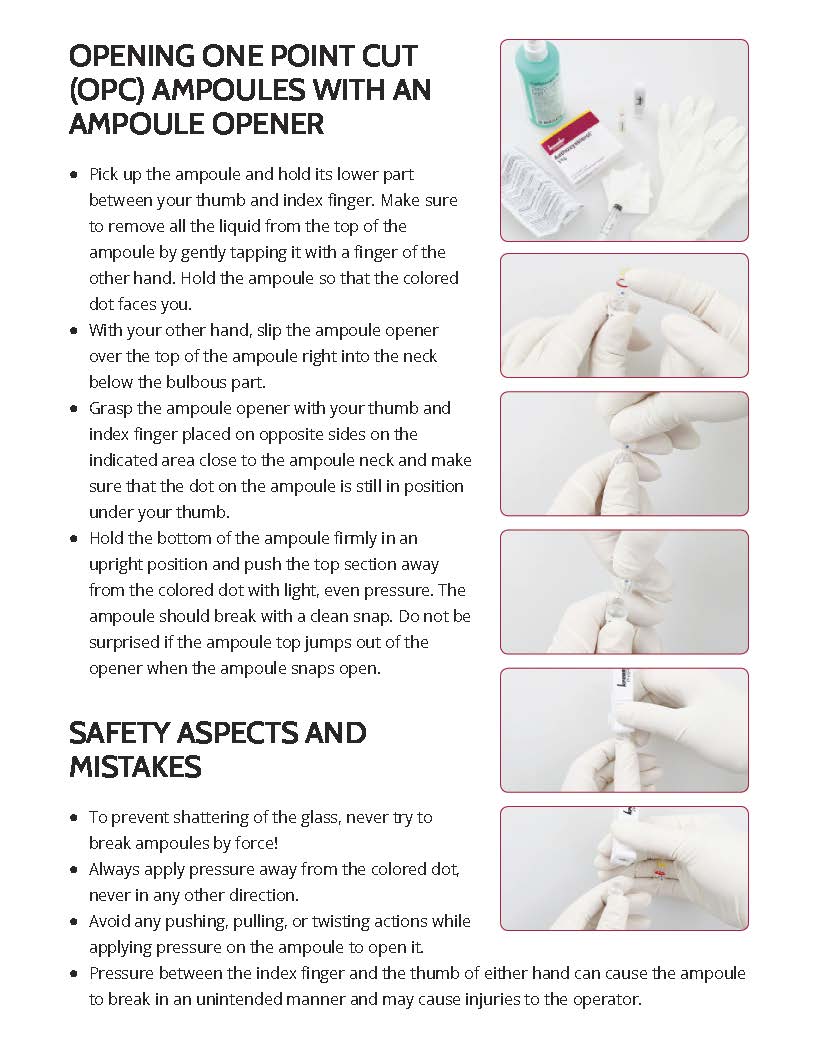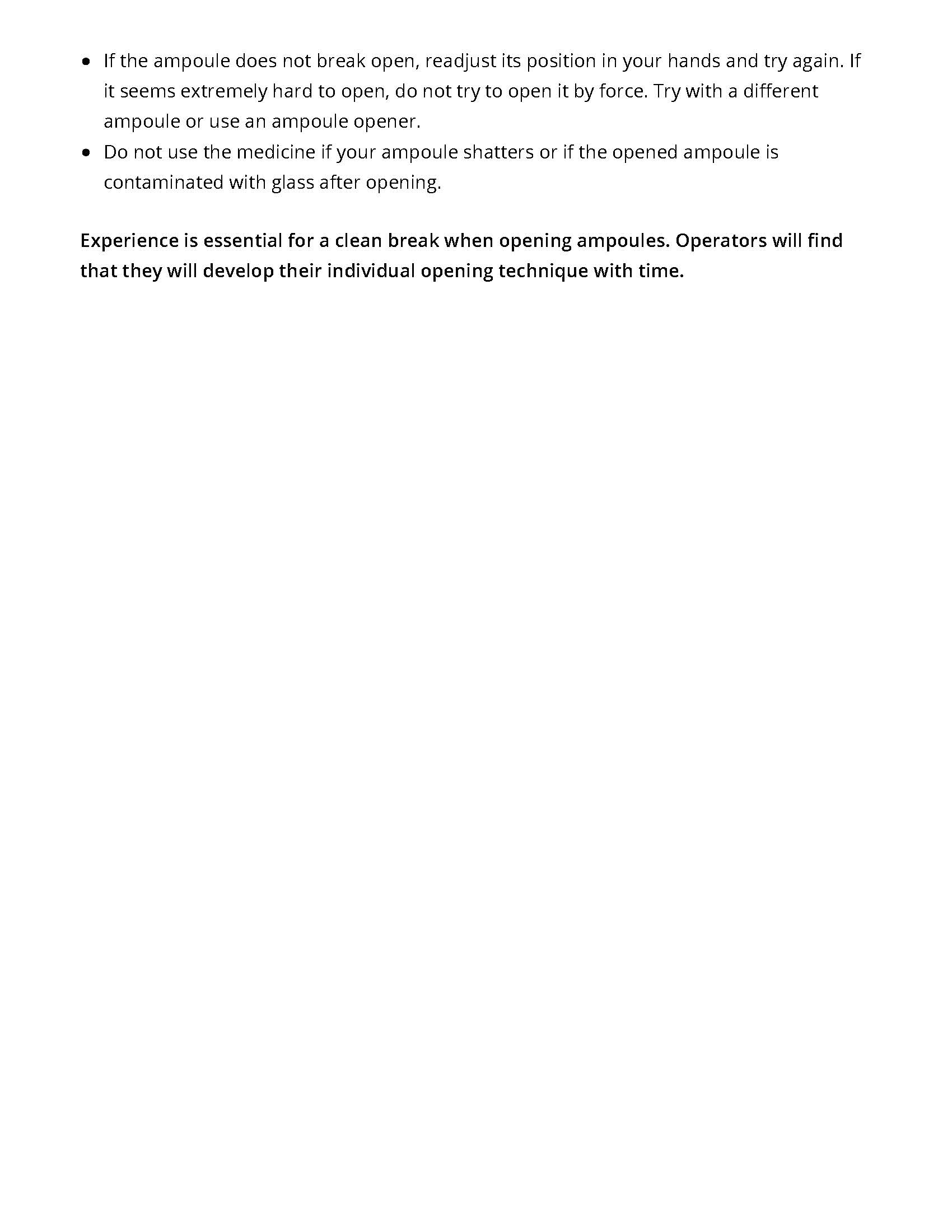 DRUG LABEL: Hexatrione
NDC: 59137-570 | Form: INJECTION, SUSPENSION
Manufacturer: Medexus Pharma, Inc.
Category: prescription | Type: HUMAN PRESCRIPTION DRUG LABEL
Date: 20260128

ACTIVE INGREDIENTS: TRIAMCINOLONE HEXACETONIDE 40 mg/2 mL
INACTIVE INGREDIENTS: SODIUM HYDROXIDE; SORBITOL SOLUTION 70%; WATER; HYDROCHLORIC ACID; BENZYL ALCOHOL; POLYSORBATE 80

Hexatrione

HOW SUPPLIED

NDC 59137-570-01

- 2 mL single-dose ampoule (40 mg/2mL). One ampoule per carton.

20 mg/mL (2 mL Ampoule) - Ampoule Label

20 mg/mL (2 mL Ampoule) - Carton Label